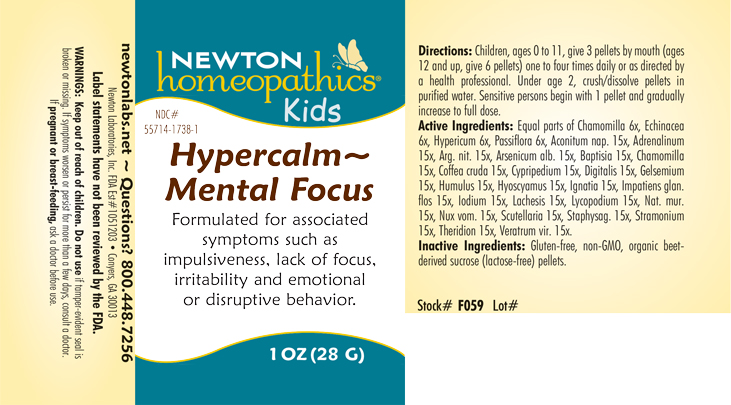 DRUG LABEL: Hypercalm-Mental Focus
NDC: 55714-1738 | Form: PELLET
Manufacturer: Newton Laboratories, Inc.
Category: homeopathic | Type: HUMAN OTC DRUG LABEL
Date: 20230630

ACTIVE INGREDIENTS: ECHINACEA, UNSPECIFIED 6 [hp_X]/1 g; GELSEMIUM SEMPERVIRENS ROOT 15 [hp_X]/1 g; PASSIFLORA INCARNATA FLOWERING TOP 6 [hp_X]/1 g; ACONITUM NAPELLUS 15 [hp_X]/1 g; EPINEPHRINE 15 [hp_X]/1 g; SILVER NITRATE 15 [hp_X]/1 g; ARSENIC TRIOXIDE 15 [hp_X]/1 g; BAPTISIA TINCTORIA ROOT 15 [hp_X]/1 g; MATRICARIA CHAMOMILLA 15 [hp_X]/1 g; ARABICA COFFEE BEAN 15 [hp_X]/1 g; CYPRIPEDIUM PARVIFLORUM VAR. PUBESCENS ROOT 15 [hp_X]/1 g; DIGITALIS 15 [hp_X]/1 g; HYOSCYAMUS NIGER 15 [hp_X]/1 g; STRYCHNOS IGNATII SEED 15 [hp_X]/1 g; IMPATIENS GLANDULIFERA FLOWER 15 [hp_X]/1 g; IODINE 15 [hp_X]/1 g; LACHESIS MUTA VENOM 15 [hp_X]/1 g; LYCOPODIUM CLAVATUM SPORE 15 [hp_X]/1 g; SODIUM CHLORIDE 15 [hp_X]/1 g; STRYCHNOS NUX-VOMICA SEED 15 [hp_X]/1 g; SCUTELLARIA LATERIFLORA WHOLE 15 [hp_X]/1 g; DELPHINIUM STAPHISAGRIA SEED 15 [hp_X]/1 g; DATURA STRAMONIUM 15 [hp_X]/1 g; THERIDION CURASSAVICUM 15 [hp_X]/1 g; VERATRUM VIRIDE ROOT 15 [hp_X]/1 g; HOPS 15 [hp_X]/1 g; HYPERICUM PERFORATUM 6 [hp_X]/1 g
INACTIVE INGREDIENTS: SUCROSE

Hypercalm 1738P

INDICATIONS AND USAGE SECTION

Formulated for associated symptoms such as impulsiveness, lack of focus, irritability and emotional or disruptive behavior.

DOSAGE & ADMINISTRATION SECTION

Directions: Children, ages 0 to 11, give 3 pellets by mouth (ages 12 and up, give 6 pellets) one to four times daily or a directed by a health professional. Under age 2, crush/dissolve pellets in purified water. Sensitive person begin with 1 pellet and gradually increase to full dose.

OTC - ACTIVE INGREDIENT SECTION

Equal parts of Chamomilla 6x, Echinacea 6x, Hypericum perforatum 6x, Passiflora incarnata 6x, Aconitum napellus 15x, Adrenalinum 15x, Argentum nitricum 15x, Arsenicum album 15x, Baptisia tinctoria 15x, Chamomilla 15x, Coffea cruda 15x, Cypripedium pubescens 15x, Digitalis purpurea 15x, Gelsemium sempervirens 15x, Humulus lupulus 15x, Hyoscyamus niger 15x, Ignatia amara 15x, Impatiens glandulifera flos 15x, Iodium 15x, Lachesis mutus 15x, Lycopodium clavatum 15x, Natrum muriaticum 15x, Nux vomica 15x, Scutellaria lateriflora 15x, Staphysagria 15x, Stramonium 15x, Theridion 15x, Veratrum viride 15x.

OTC - PURPOSE SECTION

Formulated for associated symptoms such as impulsiveness, lack of focus, irritability and emotional or disruptive behavior.

INACTIVE INGREDIENT SECTION

Gluten-free, non-GMO, organic beet-derived sucrose (lactose-free) pellets.

QUESTIONS SECTION

newtonlabs.net – Questions? 800.448.7256

Newton Laboratories, Inc. FDA Est # 1051203 - Conyers, GA 30013

WARNINGS SECTION

WARNINGS: Keep out of reach of children. Do not use if tamper-evident seal is broken or missing. If symptoms worsen or persist for more than a few days, consult a doctor. If pregnant or breast-feeding, ask a doctor before use.

OTC - PREGNANCY OR BREAST FEEDING SECTION

If pregnant or breast-feeding, ask a doctor before use.

OTC - KEEP OUT OF REACH OF CHILDREN SECTION

WARNINGS: Keep out of reach of children.